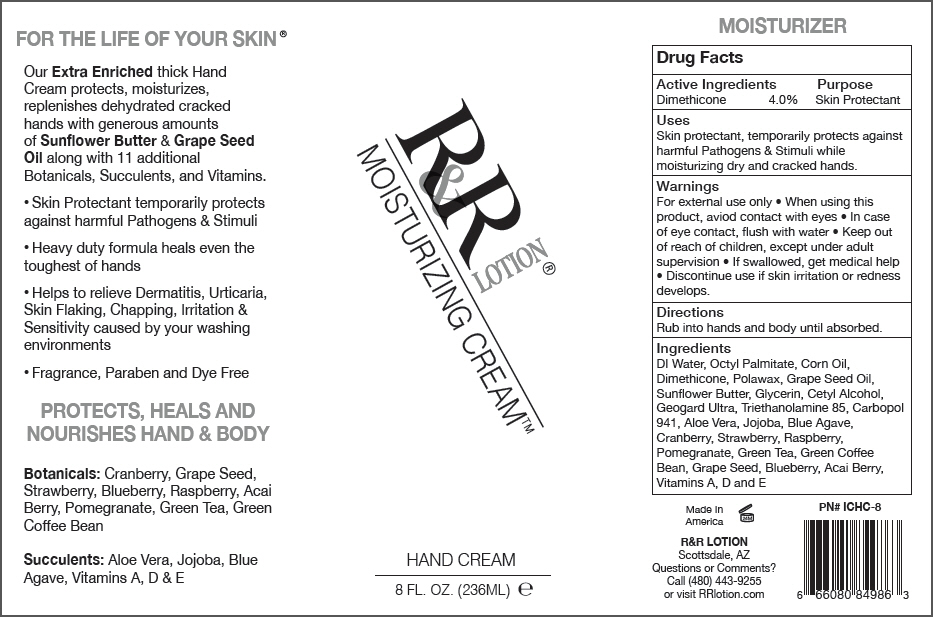 DRUG LABEL: Moisturizing Cream
NDC: 59555-801 | Form: LOTION
Manufacturer: R & R Lotion, Inc
Category: otc | Type: HUMAN OTC DRUG LABEL
Date: 20151208

ACTIVE INGREDIENTS: Dimethicone 40 mg/1 mL
INACTIVE INGREDIENTS: Water; Glycerin; Corn Oil; Gluconolactone; Sodium Benzoate; Calcium Gluconate; Carbomer Homopolymer Type A (Allyl Pentaerythritol Crosslinked); Ethylhexyl Palmitate; Grape Seed Oil; Cetyl Alcohol; .Alpha.-Tocopherol; Trolamine; vitamin A; cholecalciferol

Moisturizing Cream™

Drug Facts

Active Ingredients

Dimethicone 4.0%

Purpose

Skin Protectant

Uses

Skin protectant, temporarily protects against harmful Pathogens & Stimuli while moisturizing dry and cracked hands.

Warnings

For external use only

- When using this product, aviod contact with eyes
- In case of eye contact, flush with water

- Keep out of reach of children, except under adult supervision
- If swallowed, get medical help

- Discontinue use if skin irritation or redness develops.

Directions

Rub into hands and body until absorbed.

Ingredients

DI Water, Octyl Palmitate, Corn Oil, Dimethicone, Polawax, Grape Seed Oil, Sunflower Butter, Glycerin, Cetyl Alcohol, Geogard Ultra, Triethanolamine 85, Carbopol 941, Aloe Vera, Jojoba, Blue Agave, Cranberry, Strawberry, Raspberry, Pomegranate, Green Tea, Green Coffee Bean, Grape Seed, Blueberry, Acai Berry, Vitamins A, D and E

Questions or Comments?

Call (480) 443-9255 or visit RRlotion.com

PRINCIPAL DISPLAY PANEL - 236 ML Bottle Label

R&R LOTION®
MOISTURIZING CREAM™

HAND CREAM

8 FL. OZ. (236ML) e